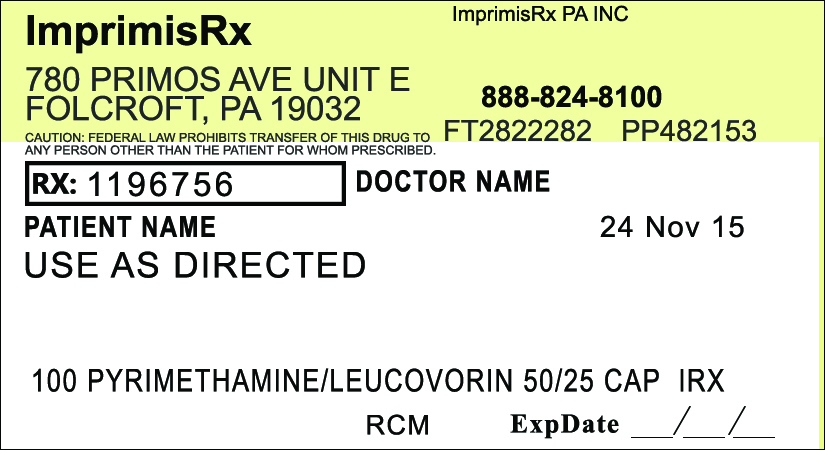 DRUG LABEL: Pyrimethamine Leucovorin
NDC: 70271-480 | Form: CAPSULE
Manufacturer: ImprimisRx PA, Inc. d/b/a ImprimisRx
Category: prescription | Type: HUMAN PRESCRIPTION DRUG LABEL
Date: 20151127

ACTIVE INGREDIENTS: PYRIMETHAMINE 50 mg/1 1; LEUCOVORIN CALCIUM 25 mg/1 1
INACTIVE INGREDIENTS: CELLULOSE, MICROCRYSTALLINE 65 mg/1 1

Pyrimethamine Leucovorin (50mg-25mg)